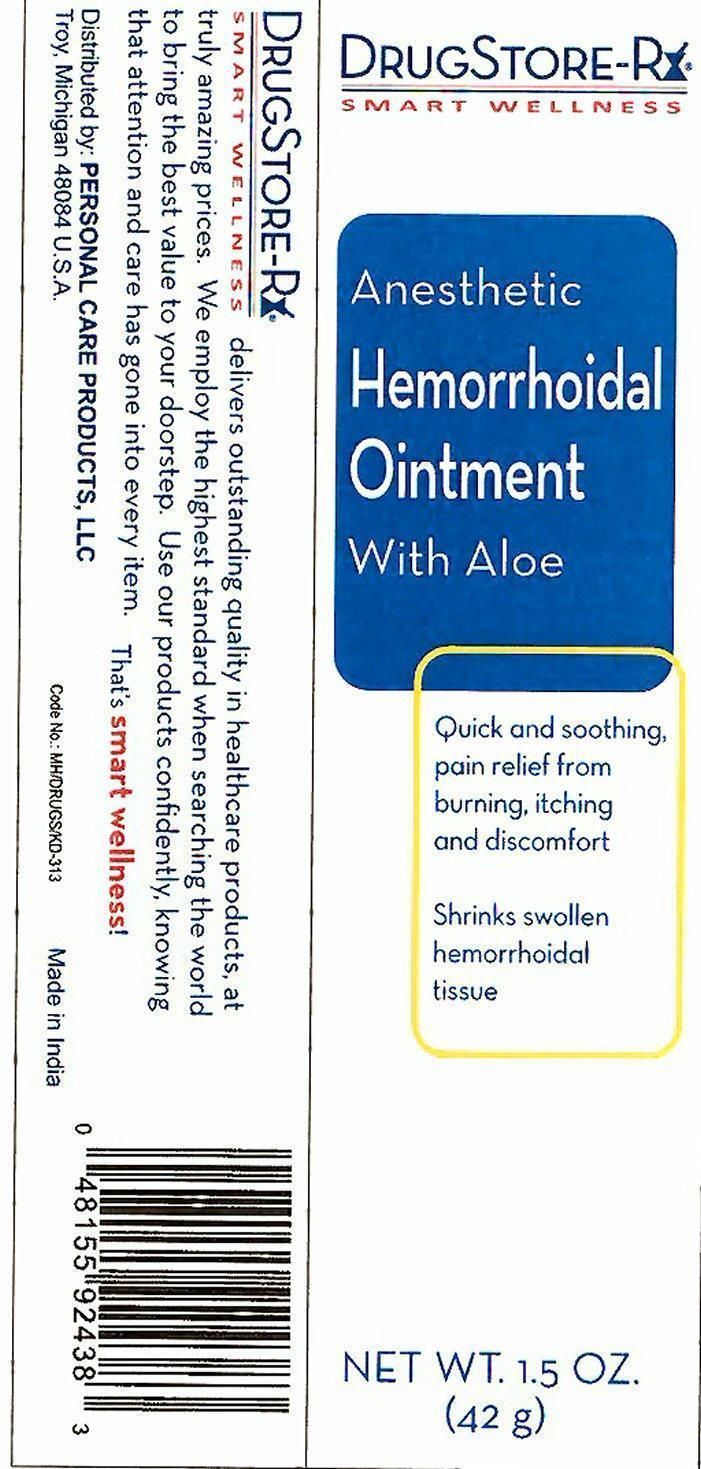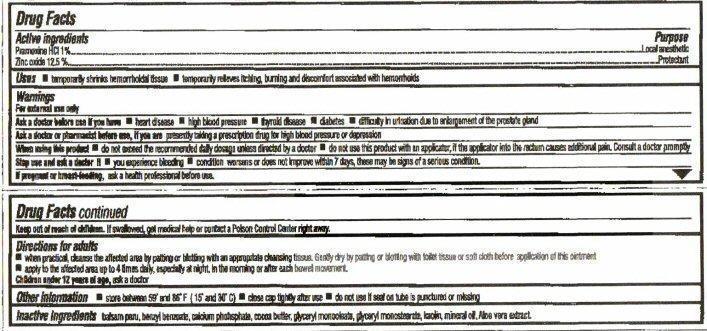 DRUG LABEL: Anesthetic Hemorrhoidal
NDC: 29500-2438 | Form: OINTMENT
Manufacturer: Personal Care Products, Inc.
Category: otc | Type: HUMAN OTC DRUG LABEL
Date: 20200723

ACTIVE INGREDIENTS: PRAMOXINE HYDROCHLORIDE 420 mg/42 g; ZINC OXIDE 5.25 g/42 g
INACTIVE INGREDIENTS: BALSAM PERU; BENZYL BENZOATE; CALCIUM PHOSPHATE; COCOA BUTTER; GLYCERYL MONOSTEARATE; KAOLIN; MINERAL OIL; GLYCERYL OLEATE

Drug Facts Active Ingredient

Pramoxine HCL 1%

Zinc oxide 12.5%

Purpose

Local anesthetic
Protectant

Keep out of reach of children. If swallowed, get medical help or contact a Poison Control Center right away.

Uses

temporarily shrinks hemorrhoidal tissue
temporarily relieves itching, burning and discomfort associated with hemorrhoids

Warnings

For external use only

Ask a doctor before use if you have - heart disease, high blood pressure, thyroid disease, diabetes, difficulty in urination due to enlargement of the prostate gland

Ask a doctor or pharmacist before use, if you are presently taking a prescription drug for high blood pressure or depression

When using this product - do not exceed the recommended daily dosage unless directed by a doctor, do not use this product with an applicator, if the applicator into the rectum causes additional pain. Consult a doctor promptly.

Stop use and ask a doctor if - you experience bleeding, condition worsens or does not improve within 7 days, these may be signs of a serious condition.

If pregnant or breast-feeding, ask a health professional before use.

Directions

Direction for adults

when practical, cleanse the affected area by patting or blotting with an appropriate cleansing tissue. Gently dry by patting or blotting with toilet tissue or soft cloth before application of this ointment, apply to the affected area up to 4 times daily, especially at night, in the morning or after each bowel movement

Children under 12 years or age, ask a doctor.

Other information

store between 59° and 86° F (15° and 30° C), close cap tightly after use, do not use if seal on tube is punctured or missing

Inactive ingredients

balsam peru, benzyl benzoate, calcium phohsphate, cocoa butter, glyceryl monostearate, glyceryl monoleate, kaolin, mineral oil, Aloe vera extract

Product Label

DRUGSTORE - Rx

SMART WELLNESS

Anesthetic Hemorrhoidal Ointment With Aloe

Quick and soothing, pain relief from burning, itching and discomfort

Shrinks swollen hemorrhoidal tissue

NET WT. 1.5 OZ. (42 g)

DRUGSTORE-Rx

SMART WELLNESS delivers outstanding quality in healthcare products, at truly amazing prices. We employ the highest standard when searching the world to bring the best value to your doorstep. Use our products confidently, knowing that attention and care has gone into every item That's smart wellness!

Distributed by: PERSONAL CARE PRODUCTS, LLC

Troy, Michigan 484084 U.S.A. Code No.MH/DRUGS/KD-313 Made in India